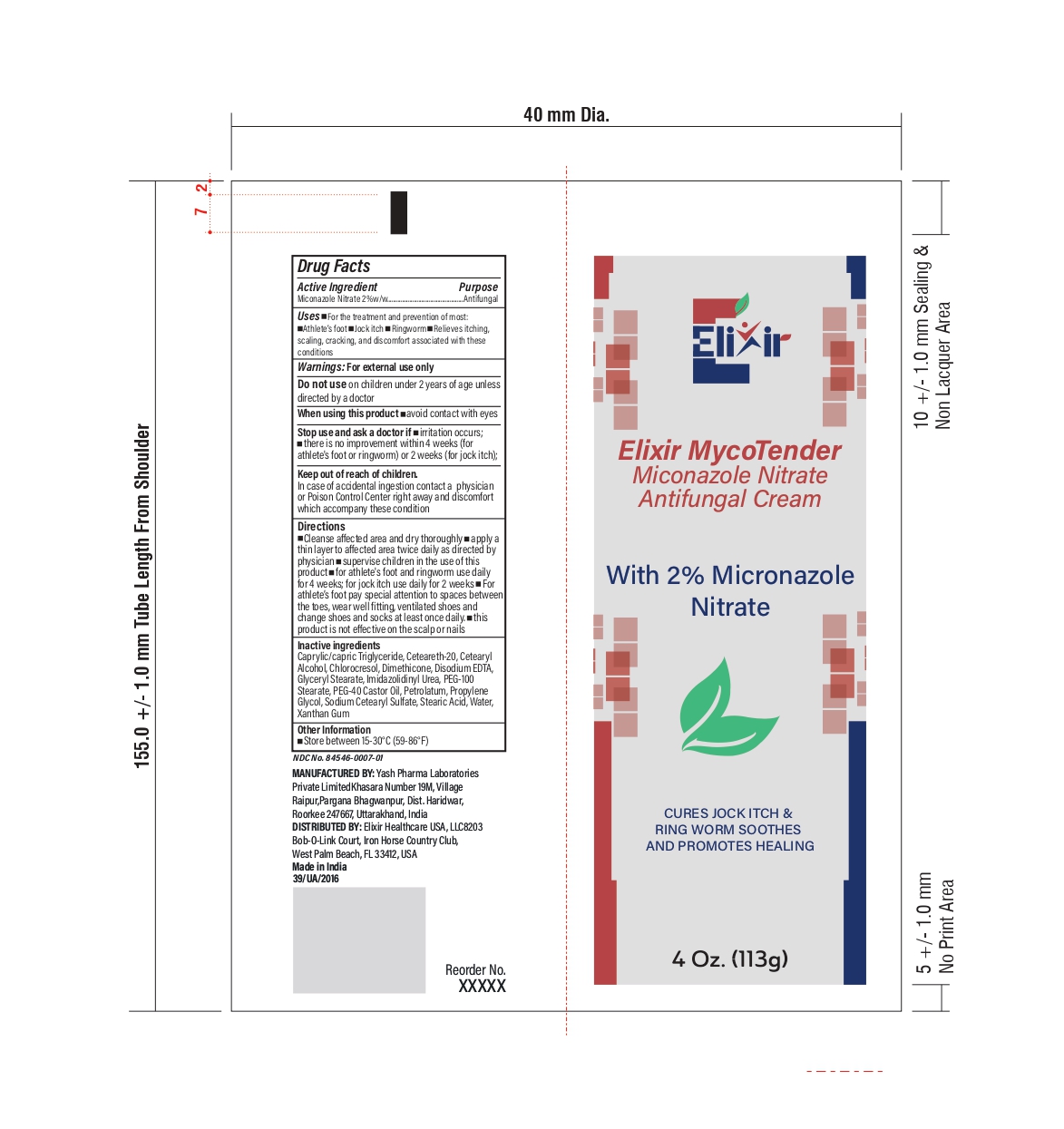 DRUG LABEL: ElixirTripleGuard

NDC: 84546-0007 | Form: CREAM
Manufacturer: ELIXIR HEALTHCARE USA, LLC.
Category: otc | Type: HUMAN OTC DRUG LABEL
Date: 20260115

ACTIVE INGREDIENTS: MICONAZOLE NITRATE 2 g/100 g
INACTIVE INGREDIENTS: CAPRYLIC/CAPRIC TRIGLYCERIDE; CETEARETH-20; CETEARYL ALCOHOL; DIMETHICONE; EDETATE DISODIUM; GLYCERYL STEARATE; IMIDAZOLIDINYL UREA; PEG-100 STEARATE; PEG-40 CASTOR OIL; PETROLATUM; PROPYLENE GLYCOL; SODIUM CETEARYL SULFATE; STEARIC ACID; WATER; XANTHAN GUM

Drug Facts

Active Ingredient (in each gram)

Miconazole Nitrate 2%w/w

Purpose

Antifungal

Uses

• For the treatment and prevention of most:
• Athlete’s foot
• Jock itch
• Ringworm
• Relieves itching, scaling, cracking, and discomfort associated with these conditions

Warnings

For external use only

Do not use

on children under 2 years of age unless directed by a doctor

When using this product

Avoid contact with eyes

Stop use and ask a doctor if

• condition persists or gets worse
• a rash or other allergic reaction develops

Keep out of reach of children

In case of accidental ingestion contact a physician or Poison Control Center right away and discomfort which accompany these conditions

Directions

Clean the affected area and dry thoroughly • Apply a thin layer of the product over affected area twice daily (morning and night) or as directed by a healthcare professional • Supervise children in the use of this product.

For athlete's foot:• Use daily for 4 weeks. If condition persists, consult a healthcare professional. • Pay special attention to the spaces between the toes •Wear well fitting, ventilated shoes • Change socks atleast once daily.

For ringworm:Use daily for 4 weeks. If condition persists, consult a healthcare professional.

For jock itch:Use daily for 2 weeks. If condition persists longer, consult a healthcare professional.

This product is not effective on the scalp or nails.

Inactive ingredients

Caprylic/capric triglyceride, Cetereath-20, Cetearyl Alcohol, Chlorocresol, Dimethicone, Disodium EDTA, Glyceryl Stearate, Imidazolidinyl Urea, PEG-100 Stearate, PEG-40 Castor Oil, Petrolatum, Propylene Glycol, Sodium Cetearyl Sulfate, Stearic Acid, Water, Xanthum Gum

Other information

• Store between 15-30°C (59-86°F)

PRINCIPAL DISPLAY PANEL

Elixir

Elixir MycoTender

Miconazole Nitrate

Antifungal Cream

With 2% Micronazole

Nitrate

CURSE JOCK ITCH &

RING WORM SOOTHES

AND PROMOTES HEALING

4 Oz. (113) g